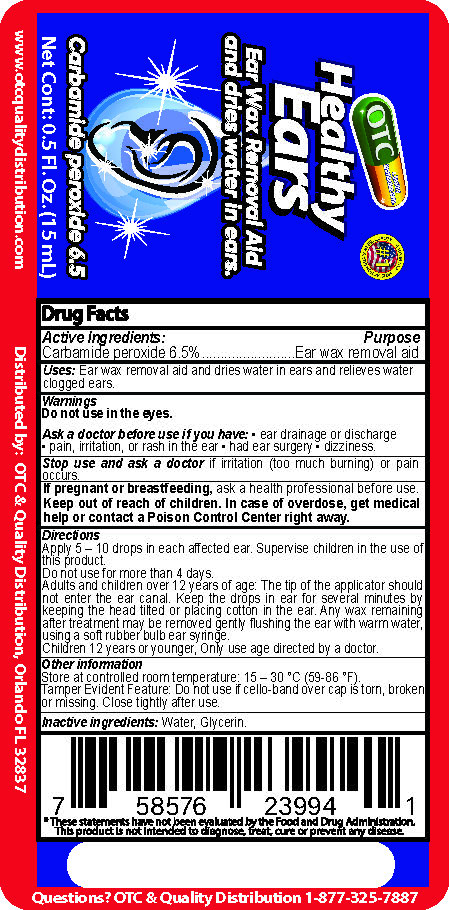 DRUG LABEL: Healthy Ears
NDC: 69469-650 | Form: SOLUTION
Manufacturer: Vitamex USA, Corp
Category: otc | Type: HUMAN OTC DRUG LABEL
Date: 20250623

ACTIVE INGREDIENTS: CARBAMIDE PEROXIDE 6.5 mg/1 mL
INACTIVE INGREDIENTS: GLYCERIN; WATER

Healthy Ears 0.5oz

Active Ingredients

Active Ingredients: Purpose

Carbamide Peroxide 6.5% Ear wax removal aid

Uses

Uses: Ear wax removal aid and dries water in ears and relives water clogged ears.

Warnings

Do not us in the eyes.

Ask a doctor before use if you have: ear drainage or discharge, pain, irritation, or rash in th ear, had ear surgery, dizziness.

Stop use and ask a doctor

Stop usa and ask a doctor if irritation (too much burning) or pain occurs.

If pregnant or breastfeeding

If preganant of breastfeeding, ask a health professional before use.

Keep out of reach of children. In case of overdose, get medical help or contact a Poison Control Center right away.

Directions

Apply 5-10 drops in each affected ear. Supervise children in the use of this product.

Do not use for more than 4 days.

Adults and children over 12 years of age: the tip of the applicator should not enter the ear canal. Keep the drops in the ear for several minutes by keeping the head tilted or placing cotton in the ear. Any wax remaining after treatment may be removed gently flushing the ear with the warm water, using soft rubber bulb ear syringe.

Children 12 years or younger, only use directed by a doctor.

Directions

Apply 5-10 drops in each affected ear. Supervise children in the use of this product.

Do not use for more than 4 days.

Adults and children over 12 years of age: the tip of the applicator should not enter the ear canal. Keep the drops in the ear for several minutes by keeping the head tilted or placing cotton in the ear. Any wax remaining after treatment may be removed gently flushing the ear with the warm water, using soft rubber bulb ear syringe.

Children 12 years or younger, only use directed by a doctor.

Other Information

Store at controlled room temperature 15-30°C (59-86°F).

Tamper Evident Feature: Do not use if cello-band over cap is torn, broken or missing. Close tightly after use.

Inactive Ingredients

Inactive ingredients: Water, Glycerin.

Keep out of reach children

Keep out of reach of children

Healthy Ears 0.5oz

Healthy Ears

Ear wax removal aid and dries water in ears

Carbamide Peroxide 6.5%

Net Cont: 0.5 fl oz (15mL)